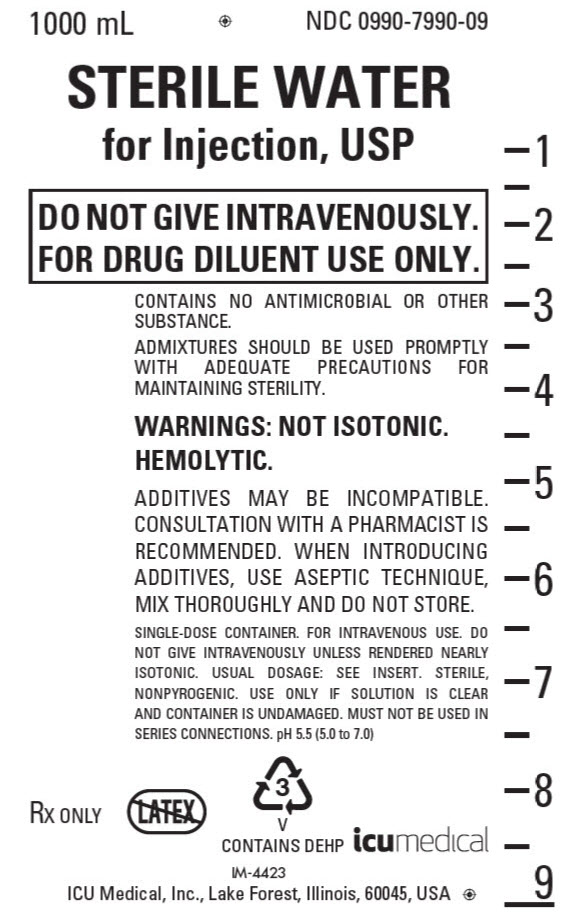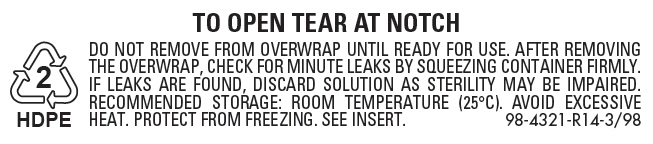 DRUG LABEL: Sterile Water
NDC: 0990-7990 | Form: INJECTION, SOLUTION
Manufacturer: ICU Medical Inc.
Category: prescription | Type: HUMAN PRESCRIPTION DRUG LABEL
Date: 20251102

ACTIVE INGREDIENTS: WATER 1000 mL/1000 mL

Sterile Water for Injection, USP

FOR DRUG DILUENT USE ONLY

Flexible Plastic Container

Rx only

DESCRIPTION

Sterile Water for Injection, USP is a sterile, nonpyrogenic, solute-free preparation of distilled water for injection. It is for use only as a sterile solvent or diluent vehicle for drugs or solutions suitable for parenteral administration. The pH is 5.5 (5.0 to 7.0).

Sterile Water for Injection contains no bacteriostat, antimicrobial agent or added buffer and is intended only for single-dose injection after admixture with an appropriate solute or solution. When smaller amounts are required, the unused portion should be discarded.

Sterile Water for Injection is a pharmaceutic aid (vehicle) and parenteral fluid replenisher after addition of an appropriate solute.

Water for Injection, USP is chemically designated H2O.

The flexible plastic container is fabricated from a specially formulated polyvinylchloride. Water can permeate from inside the container into the overwrap but not in amounts sufficient to affect the solution significantly. Solutions inside the plastic container also can leach out certain chemical components of the plastic in very small amounts before the expiration period is attained. However, the safety of the plastic has been confirmed by tests in animals according to USP biological standards for plastic containers.

CLINICAL PHARMACOLOGY

When administered intravenously as a vehicle for drugs, sterile water for injection provides a source of water for parenteral fluid replenishment after sufficient solute is introduced to achieve an osmolarity of 112 mOsmol or more per liter.

Water is an essential constituent of all body tissues and accounts for approximately 70% of total body weight. Average normal adult daily requirement ranges from two to three liters (1.0 to 1.5 liters each for insensible water loss by perspiration and urine production).

Water balance is maintained by various regulatory mechanisms. Water distribution depends primarily on the concentration of electrolytes in the body compartments and sodium (Na^+) plays a major role in maintaining physiologic equilibrium.

INDICATIONS AND USAGE

Sterile Water for Injection, USP is indicated for use only as a solvent or diluent vehicle for parenterally administered drugs or solutions and as a source of water for parenteral fluid replenishment after suitable additives are introduced.

For intravenous administration, an osmolar concentration not less than two-fifths (0.4) of the normal osmolarity of the extracellular fluid (280 mOsmol/liter) is essential to avoid intravascular hemolysis.

CONTRAINDICATIONS

Do not administer without the addition of a solute.

WARNINGS

FOR DRUG DILUENT USE ONLY.

Intravenous administration of Sterile Water for Injection, USP without additives may result in hemolysis.

The intravenous administration of sterile water for injection with additives can cause fluid and/or solute overloading resulting in dilution of serum electrolyte concentrations, overhydration, congested states or pulmonary edema. The risk of dilutional states is inversely proportional to the electrolyte concentrations of administered parenteral solutions. The risk of solute overload causing congested states with peripheral and pulmonary edema is directly proportional to the electrolyte concentrations of such solutions.

WARNING: This product contains aluminum that may be toxic. Aluminum may reach toxic levels with prolonged parenteral administration if kidney function is impaired. Premature neonates are particularly at risk because their kidneys are immature, and they require large amounts of calcium and phosphate solutions, which contain aluminum.

Research indicates that patients with impaired kidney function, including premature neonates, who receive parenteral levels of aluminum at greater than 4 to 5 mcg/kg/day accumulate aluminum at levels associated with central nervous system and bone toxicity. Tissue loading may occur at even lower rates of administration.

PRECAUTIONS

Do not use for intravenous injection unless the osmolar concentration of additives totals at least 112 mOsmol/liter (two-fifths of the normal osmolarity of the extracellular fluid — 280 mOsmol/liter).

Do not administer unless solution is clear and container is undamaged. Discard unused portion.

Pregnancy Category C: Animal reproduction studies have not been conducted with sterile water for injection. It is also not known whether sterile water containing additives can cause fetal harm when administered to a pregnant woman or can affect reproduction capacity. Sterile water for injection with additives should be given to a pregnant woman only if clearly needed.

Pediatric Use: The safety and effectiveness in the pediatric population are based on the similarity of the clinical conditions of the pediatric and adult populations. In neonates or very small infants the volume of fluid may affect fluid and electrolyte balance.

This product contains no more than 25 mcg/L of aluminum.

ADVERSE REACTIONS

Reactions which may occur because of the technique of administration include febrile response, infection at the site of injection, venous thrombosis or phlebitis extending from the site of injection, extravasation and hypervolemia.

If an adverse reaction does occur, discontinue the infusion, evaluate the patient, institute appropriate therapeutic countermeasures and save the remainder of the fluid for examination if deemed necessary.

OVERDOSAGE

In the event of overhydration or solute overload, re-evaluate the patient and institute appropriate corrective measures. (See WARNINGS.)

DOSAGE AND ADMINISTRATION

Following suitable admixture of prescribed additive, the dose is usually dependent upon the age, weight and clinical condition of the patient.

Drug Interactions

Additives may be incompatible. Consult with pharmacist, if available. When introducing additives, use aseptic technique, mix thoroughly and do not store.

Parenteral drug products should be inspected visually for particulate matter and discoloration prior to administration, whenever solution and container permit. (See PRECAUTIONS).

HOW SUPPLIED

Sterile Water for Injection, USP is supplied in a single-dose 1000 mL flexible plastic container (NDC 0409-7990-09 [Manufactured by ICU Medical, Inc., Lake Forest, Illinois, 60045, USA] , [Manufactured for ICU Medical, Inc., Lake Forest, Illinois, 60045, USA] and 0990-7990-09,).

ICU Medical is transitioning NDC codes from the "0409" to a "0990" labeler code. Both NDC codes are expected to be in the market for a period of time.

INSTRUCTIONS FOR USE

To Open

Tear outer wrap at notch and remove solution container. If supplemental medication is desired, follow directions below before preparing for administration. Some opacity of the plastic due to moisture absorption during the sterilization process may be observed. This is normal and does not affect the solution quality or safety. The opacity will diminish gradually.

To Add Medication

1. Prepare additive port.
2. Using aseptic technique and an additive delivery needle of appropriate length, puncture resealable additive port at target area, inner diaphragm and inject. Withdraw needle after injecting medication.
3. The additive port may be protected by covering with an additive cap.
4. Mix container contents thoroughly.

Preparation for Administration

(Use aseptic technique)

1. Close flow control clamp of administration set.
2. Remove cover from outlet port at bottom of container.
3. Insert piercing pin of administration set into port with a twisting motion until the set is firmly seated. NOTE: See full directions on administration set carton.
4. Suspend container from hanger.
5. Squeeze and release drip chamber to establish proper fluid level in chamber.
6. Open flow control clamp and clear air from set. Close clamp.
7. Attach set to venipuncture device. If device is not indwelling, prime and make venipuncture.
8. Regulate rate of administration with flow control clamp.

WARNING: DO NOT USE FLEXIBLE CONTAINER IN SERIES CONNECTIONS.

Store at 20 to 25°C (68 to 77°F). [See USP Controlled Room Temperature.] Protect from freezing.

Revised: September, 2018

ICU Medical, Inc., Lake Forest, Illinois, 60045, USA EN-4689

PRINCIPAL DISPLAY PANEL - 1000 mL Bag Label

1000 mL

NDC 0990-7990-09

STERILE WATER
for Injection, USP

DO NOT GIVE INTRAVENOUSLY.
FOR DRUG DILUENT USE ONLY.

CONTAINS NO ANTIMICROBIAL OR OTHER
SUBSTANCE.

ADMIXTURES SHOULD BE USED PROMPTLY
WITH ADEQUATE PRECAUTIONS FOR
MAINTAINING STERILITY.

WARNINGS: NOT ISOTONIC.
HEMOLYTIC.

ADDITIVES MAY BE INCOMPATIBLE.
CONSULTATION WITH A PHARMACIST IS
RECOMMENDED. WHEN INTRODUCING
ADDITIVES, USE ASEPTIC TECHNIQUE,
MIX THOROUGHLY AND DO NOT STORE.

SINGLE-DOSE CONTAINER. FOR INTRAVENOUS USE. DO
NOT GIVE INTRAVENOUSLY UNLESS RENDERED NEARLY
ISOTONIC. USUAL DOSAGE: SEE INSERT. STERILE,
NONPYROGENIC. USE ONLY IF SOLUTION IS CLEAR
AND CONTAINER IS UNDAMAGED. MUST NOT BE USED IN
SERIES CONNECTIONS. pH 5.5 (5.0 to 7.0)

RX ONLY

3
V
CONTAINS DEHP

icumedical

IM-4423

ICU Medical, Inc., Lake Forest, Illinois, 60045, USA

PRINCIPAL DISPLAY PANEL - 1000 mL Bag Overwrap

2
HDPE

TO OPEN TEAR AT NOTCH

DO NOT REMOVE FROM OVERWRAP UNTIL READY FOR USE. AFTER REMOVING
THE OVERWRAP, CHECK FOR MINUTE LEAKS BY SQUEEZING CONTAINER FIRMLY.
IF LEAKS ARE FOUND, DISCARD SOLUTION AS STERILITY MAY BE IMPAIRED.
RECOMMENDED STORAGE: ROOM TEMPERATURE (25°C). AVOID EXCESSIVE
HEAT. PROTECT FROM FREEZING. SEE INSERT.
98-4321-R14-3/98